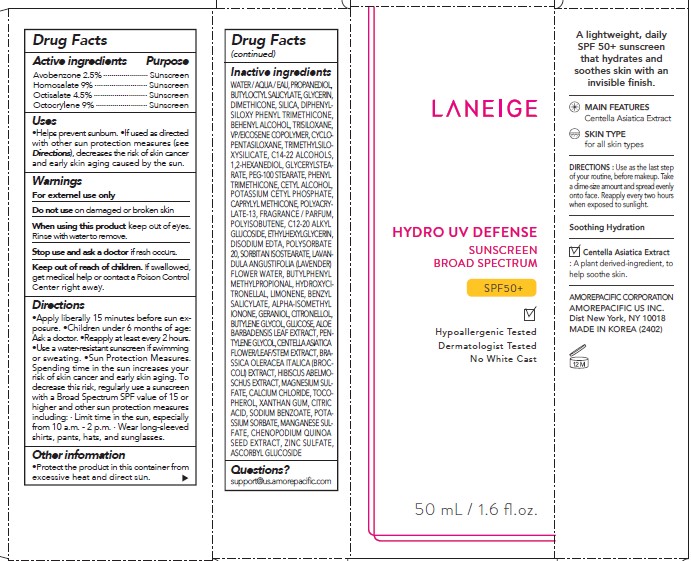 DRUG LABEL: Laneige Hydro UV Defense
NDC: 43419-768 | Form: LOTION
Manufacturer: Amorepacific Corporation
Category: otc | Type: HUMAN OTC DRUG LABEL
Date: 20230110

ACTIVE INGREDIENTS: OCTISALATE 2.25 g/50 mL; AVOBENZONE 1.25 g/50 mL; HOMOSALATE 4.5 g/50 mL; OCTOCRYLENE 4.5 g/50 mL
INACTIVE INGREDIENTS: BENZYL SALICYLATE; ISOMETHYL-.ALPHA.-IONONE; GERANIOL; PROPANEDIOL; MAGNESIUM SULFATE, UNSPECIFIED; ZINC SULFATE; SORBITAN ISOSTEARATE; PHENYL TRIMETHICONE; CETYL ALCOHOL; CAPRYLYL TRISILOXANE; ETHYLHEXYLGLYCERIN; .BETA.-CITRONELLOL, (R)-; ALOE VERA LEAF; CALCIUM CHLORIDE; TOCOPHEROL; CITRIC ACID MONOHYDRATE; ABELMOSCHUS MOSCHATUS SEED; POLYISOBUTYLENE (85000 MW); C12-20 ALKYL GLUCOSIDE; DIPHENYLSILOXY PHENYL TRIMETHICONE; GLYCERYL MONOSTEARATE; POTASSIUM CETYL PHOSPHATE; EDETATE DISODIUM; POLYSORBATE 20; LAVENDER OIL; XANTHAN GUM; SODIUM BENZOATE; POTASSIUM SORBATE; MANGANESE SULFATE; ASCORBYL GLUCOSIDE; CYCLOMETHICONE 5; C14-22 ALCOHOLS; BUTYLPHENYL METHYLPROPIONAL; BUTYLOCTYL SALICYLATE; ANHYDROUS DEXTROSE; CENTELLA ASIATICA FLOWERING TOP; BROCCOLI SPROUT; WATER; SILICON DIOXIDE; DOCOSANOL; TRISILOXANE; HYDROXYCITRONELLAL; GLYCERIN; DIMETHICONE; BUTYLENE GLYCOL; PENTYLENE GLYCOL; VINYLPYRROLIDONE/EICOSENE COPOLYMER; TRIMETHYLSILOXYSILICATE (M/Q 0.8-1.0); 1,2-HEXANEDIOL; PEG-100 STEARATE; LIMONENE, (+)-

Laneige Hydro UV Defense Broad Spectrum SPF 50+

Drug Facts

Inactive ingredients

WATER / AQUA / EAU, PROPANEDIOL, BUTYLOCTYL SALICYLATE, GLYCERIN, DIMETHICONE, SILICA, DIPHENYLSILOXY PHENYL TRIMETHICONE, BEHENYL ALCOHOL, TRISILOXANE, VP/EICOSENE COPOLYMER, CYCLOPENTASILOXANE, TRIMETHYLSILOXYSILICATE, C14-22 ALCOHOLS, 1,2-HEXANEDIOL, GLYCERYLSTEARATE, PEG-100 STEARATE, PHENYL TRIMETHICONE, CETYL ALCOHOL, POTASSIUM CETYL PHOSPHATE, CAPRYLYL METHICONE, POLYACRYLATE-13, FRAGRANCE / PARFUM, POLYISOBUTENE, C12-20 ALKYL GLUCOSIDE, ETHYLHEXYLGLYCERIN, DISODIUM EDTA, POLYSORBATE 20, SORBITAN ISOSTEARATE, LAVANDULA ANGUSTIFOLIA (LAVENDER) FLOWER WATER, BUTYLPHENYL METHYLPROPIONAL, HYDROXYCITRONELLAL, LIMONENE, BENZYL SALICYLATE, ALPHA-ISOMETHYL IONONE, GERANIOL, CITRONELLOL, BUTYLENE GLYCOL, GLUCOSE, ALOE BARBADENSIS LEAF EXTRACT, PENTYLENE GLYCOL, CENTELLA ASIATICA FLOWER/LEAF/STEM EXTRACT, BRASSICA OLERACEA ITALICA (BROCCOLI) EXTRACT, HIBISCUS ABELMOSCHUS EXTRACT, MAGNESIUM SULFATE, CALCIUM CHLORIDE, TOCOPHEROL, XANTHAN GUM, CITRIC ACID, SODIUM BENZOATE, POTASSIUM SORBATE, MANGANESE SULFATE, CHENOPODIUM QUINOA SEED EXTRACT, ZINC SULFATE, ASCORBYL GLUCOSIDE

ACTIVE INGREDIENTS

Avobenzone 2.5%
Homosalate 9%
Octisalate 4.5%
Octocrylene 9%

PURPOSE

Sunscreen

USES

- Helps prevent sunburn
- If used as directed with other sun protection measures (see Directions), decreases the risk of skin cancer and early skin aging caused by the sun

WARNINGS

- For external use only

- Do not use on damaged or broken skin.

- When using this product keep out of eyes. Rinse with water to remove.

- Stop use and ask a doctor if rash occurs.

- Keep out of reach of children. If swallowed, get medical help or contact a Poison Control Center right away.

DIRECTIONS

- Apply liberally 15 minutes before sun exposure
- Reapply at least every 2 hours.
- Use a water-resistant sunscreen if swimming or sweating.
- Sun Protection Measures. Spending time in the sun increases your risk of skin cancer and early skin aging. To decrease this risk, regularly use a sunscreen with a Broad Spectrum SPF value of 15 or higher and other sun protection measures including :
  - Limit time in the sun, especially from 10 a.m. - 2 p.m.
- Wear long-sleeved shirts, pants, hats, and sunglasses.
- Children under 6 months of age : Ask a doctor.

OTHER INFORMATION

- Protect the product in this container from excessive heat and direct sun

INACTIVE INGREDIENTS

WATER / AQUA / EAU, DIMETHICONE, CYCLOPENTASILOXANE, BUTYLENE GLYCOL, PROPYLHEPTYL CAPRYLATE, CETYL PEG/PPG-10/1 DIMETHICONE, CAPRYLIC/CAPRIC TRIGLYCERIDE, DIMETHICONE/VINYL DIMETHICONE CROSSPOLYMER, PROPANEDIOL, POLYSILICONE-11, DISTEARDIMONIUM HECTORITE, VINYL DIMETHICONE/METHICONE SILSESQUIOXANE CROSSPOLYMER, SYNTHETIC FLUORPHLOGOPITE, HDI/TRIMETHYLOL HEXYLLACTONE CROSSPOLYMER, 1,2-HEXANEDIOL, MAGNESIUM SULFATE, POLYHYDROXYSTEARIC ACID, METHYL METHACRYLATE CROSSPOLYMER, ALUMINA, FRAGRANCE / PARFUM, STEARIC ACID, CAPRYLYL DIMETHICONE ETHOXY GLUCOSIDE, CAPRYLYL GLYCOL, GLYCERYL CAPRYLATE, SOLIDAGO VIRGAUREA (GOLDENROD) EXTRACT, EUGENIA CARYOPHYLLUS (CLOVE) BUD EXTRACT, ETHYLHEXYLGLYCERIN, DICAPRYLYL CARBONATE, MICA, SILICA, TOCOPHEROL, IRON OXIDES (CI 77491), TRIETHOXYCAPRYLYLSILANE

Questions?

support@us.amorepacific.com

PRINCIPAL DISPLAY PANEL

Laneige

Hydro UV Defense

Sunscreen

Broad Spectrum

SPF 50+

Hypoallergenic Tested

Dermatologist Tested

No White Cast

50 ml / 1.6 fl. oz.